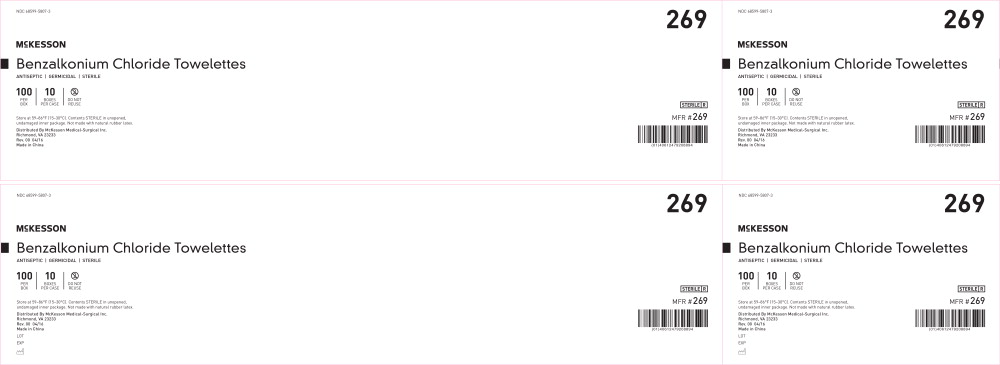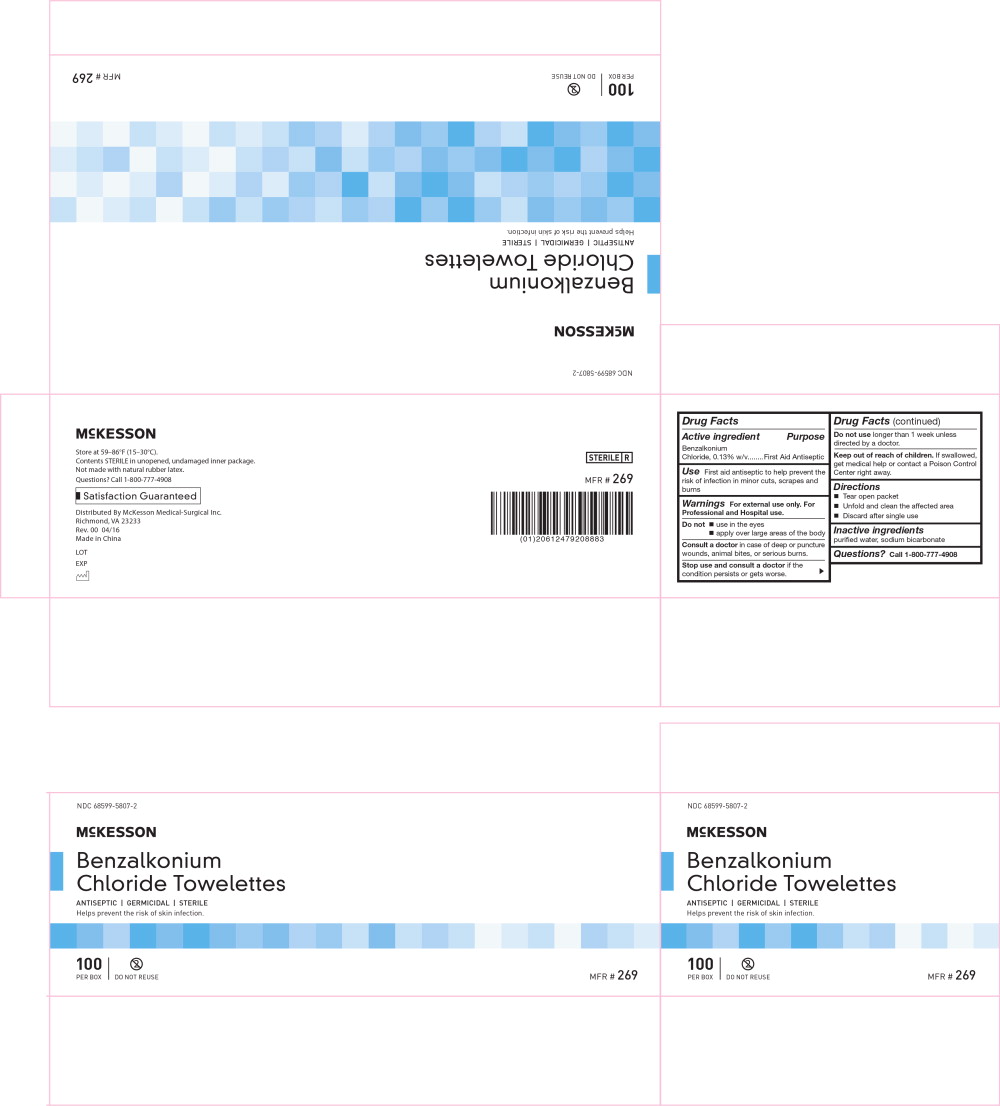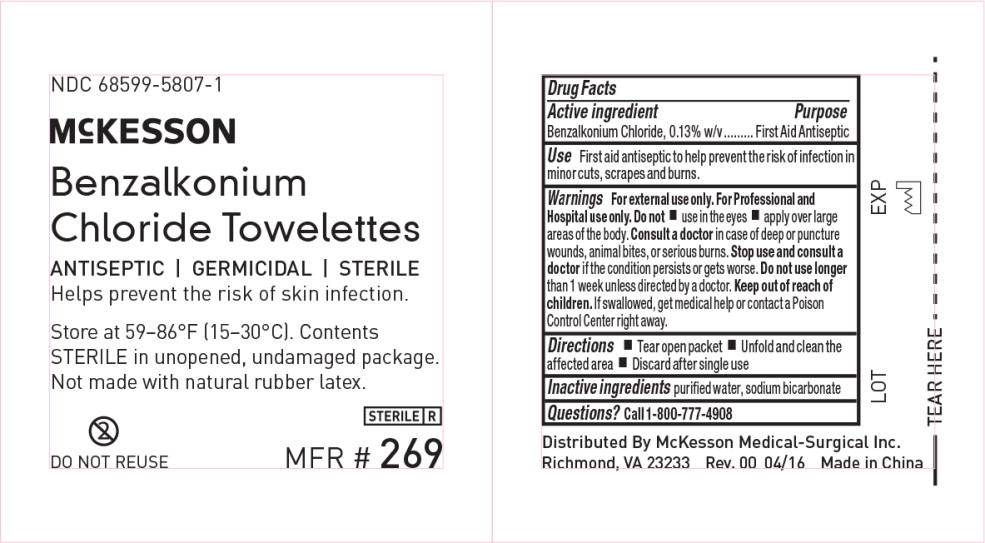 DRUG LABEL: McKesson Benzalkonium Chloride Towelette
NDC: 68599-5807 | Form: SWAB
Manufacturer: McKesson Medical-Surgical
Category: otc | Type: HUMAN OTC DRUG LABEL
Date: 20241011

ACTIVE INGREDIENTS: BENZALKONIUM CHLORIDE 0.13 g/100 g
INACTIVE INGREDIENTS: WATER; SODIUM BICARBONATE

Drug Facts

Active ingredient

Benzalkonium Chloride, 0.13% w/v

Purpose

First Aid Antiseptic

Use

Towelette to help prevent the risk of skin infection.

Warnings

For external use only.

Do not insert

- into the vagina.

Do not

- use in the eyes or apply over large areas of the body.

ASK DOCTOR

Consult a doctorin case of deep or puncture wounds, animal bites, or serious burns. Stop use and consult a doctor if the condition persists or gets worse.

Do not use longerthan 1 week unless directed by a doctor.

Keep out of reach of children.If swallowed, get medical help or contact a Poison Control Center right away.

Directions

- Tear open packet
- Unfold and clean the affected area
- Discard after single use

Inactive ingredients

water, sodium bicarbonate

Questions?

Call 1-800-777-4908

Principal Display Panel - 0.13 g/100 g Case Label

NDC 68599-5807-3

269

McKESSON

Benzalkonium Chloride Towelettes

ANTISEPTIC | GERMICIDAL | STERILE

100

PER BOX

10

BOXES PER CASE

DO NOT REUSE

Store at 59–86°F (15–30°C). Contents STERILE in unopened, undamaged inner package. Not made with natural rubber latex.

Distributed By McKesson Medical-Surgical Inc.

Richmond, VA 23233

Rev. 00 04/16

Made in China

STERILE R

MFR # 269

Principal Display Panel - 0.13 g/100 g Box Label

NDC 68599-5807-2

McKESSON

Benzalkonium
Chloride Towelettes

ANTISEPTIC | GERMICIDAL | STERILE

Helps prevent the risk of skin infection.

100

PER BOX

DO NOT REUSE

MFR # 269

Principal Display Panel - 0.13 g/100 g Packet Label

NDC 68599-5807-1

McKESSON

Benzalkonium
Chloride Towelettes

ANTISEPTIC | GERMICIDAL | STERILE

Helps prevent the risk of skin infection.

Store at 59–86°F (15–30°C). Contents

STERILE in unopened, undamaged package.

Not made with natural rubber latex.

DO NOT REUSE

STERILE R

MFR # 269